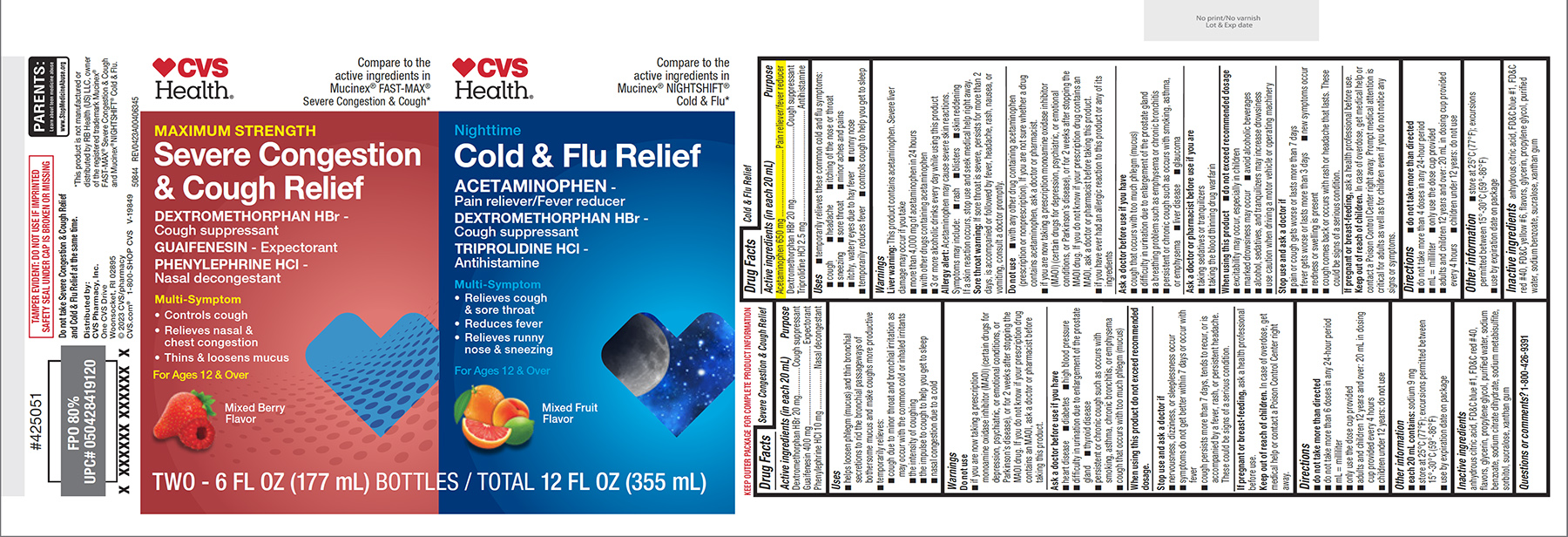 DRUG LABEL: Severe Congestion, Cough, Cold and Flu Relief
NDC: 51316-463 | Form: KIT | Route: ORAL
Manufacturer: CVS WOONSOCKET PRESCRIPTION CENTER, INCORPORATED
Category: otc | Type: HUMAN OTC DRUG LABEL
Date: 20251017

ACTIVE INGREDIENTS: DEXTROMETHORPHAN HYDROBROMIDE 20 mg/20 mL; GUAIFENESIN 400 mg/20 mL; PHENYLEPHRINE HYDROCHLORIDE 10 mg/20 mL; ACETAMINOPHEN 650 mg/20 mL; DEXTROMETHORPHAN HYDROBROMIDE 20 mg/20 mL; TRIPROLIDINE HYDROCHLORIDE 2.5 mg/20 mL
INACTIVE INGREDIENTS: ANHYDROUS CITRIC ACID; FD&C BLUE NO. 1; FD&C RED NO. 40; GLYCERIN; PROPYLENE GLYCOL; WATER; SODIUM BENZOATE; TRISODIUM CITRATE DIHYDRATE; SODIUM METABISULFITE; SORBITOL; SUCRALOSE; XANTHAN GUM; ANHYDROUS CITRIC ACID; FD&C BLUE NO. 1; FD&C RED NO. 40; FD&C YELLOW NO. 6; GLYCERIN; PROPYLENE GLYCOL; WATER; SODIUM BENZOATE; SUCRALOSE; XANTHAN GUM

CVS 44-004063

Active ingredients (in each 20 mL)

Dextromethorphan HBr 20 mg
Guaifenesin 400 mg
Phenylephrine HCl 10 mg

Purpose

Cough suppressant
Expectorant
Nasal decongestant

Uses

- helps loosen phlegm (mucus) and thin bronchial secretions to rid the bronchial passageways of bothersome mucus and make coughs more productive
- temporarily relieves:
  - cough due to minor throat and bronchial irritation as may occur with the common cold or inhaled irritants
  - the intensity of coughing
  - the impulse to cough to help you get to sleep
  - nasal congestion due to a cold

Warnings

Do not use

- if you are now taking a prescription monoamine oxidase inhibitor (MAOI) (certain drugs for depression, psychiatric, or emotional conditions, or Parkinson’s disease), or for 2 weeks after stopping the MAOI drug. If you do not know if your prescription drug contains an MAOI, ask a doctor or pharmacist before taking this product.

Ask a doctor before use if you have

- heart disease
- diabetes
- high blood pressure
- difficulty in urination due to enlargement of the prostate gland
- thyroid disease
- persistent or chronic cough such as occurs with smoking, asthma, chronic bronchitis, or emphysema
- cough that occurs with too much phlegm (mucus)

When using this product

do not exceed recommended dosage.

Stop use and ask a doctor if

- nervousness, dizziness, or sleeplessness occur
- symptoms do not get better within 7 days or occur with fever
- cough persists more than 7 days, tends to recur, or is accompanied by a fever, rash, or persistent headache. These could be signs of a serious condition.

If pregnant or breast-feeding,

ask a health professional before use.

Keep out of reach of children.

In case of overdose, get medical help or contact a Poison Control Center right away.

Directions

- do not take more than directed
- do not take more than 6 doses in any 24-hour period
- mL = milliliter
- only use the dose cup provided
- adults and children 12 years and over: 20 mL in dosing cup provided every 4 hours
- children under 12 years: do not use

Other information

- each 20 mL contains: sodium 9 mg
- store at 25°C (77°F); excursions permitted between 15°-30°C (59°-86°F)
- use by expiration date on package

Inactive ingredients

anhydrous citric acid, FD&C blue #1, FD&C red #40, flavors, glycerin, propylene glycol, purified water, sodium benzoate, sodium citrate dihydrate, sodium metabisulfite, sorbitol, sucralose, xanthan gum

Questions or comments?

1-800-426-9391

Active ingredients (in each 20 mL)

Acetaminophen 650 mg
Dextromethorphan HBr 20 mg
Triprolidine HCl 2.5 mg

Purpose

Pain reliever/fever reducer
Cough suppressant
Antihistamine

Uses

- temporarily relieves these common cold and flu symptoms:
  - cough
  - headache
  - runny nose
  - sneezing
  - sore throat
  - itchy, watery eyes due to hay fever
  - itching of the nose or throat
  - minor aches and pains
- temporarily reduces fever
- controls cough to help you get to sleep

Warnings

Liver warning: This product contains acetaminophen. Severe liver damage may occur if you take

- more than 4,000 mg of acetaminophen in 24 hours
- with other drugs containing acetaminophen
- 3 or more alcoholic drinks every day while using this product

Allergy alert: Acetaminophen may cause severe skin reactions. Symptoms may include:

- rash
- blisters
- skin reddening

If a skin reaction occurs, stop use and seek medical help right away.

Sore throat warning: If sore throat is severe, persists for more than 2 days, is accompanied or followed by fever, headache, rash, nausea, or vomiting, consult a doctor promptly.

Do not use

- with any other drug containing acetaminophen (prescription or nonprescription). If you are not sure whether a drug contains acetaminophen, ask a doctor or pharmacist.
- if you are now taking a prescription monoamine oxidase inhibitor (MAOI) (certain drugs for depression, psychiatric, or emotional conditions, or Parkinson’s disease), or for 2 weeks after stopping the MAOI drug. If you do not know if your prescription drug contains an MAOI, ask a doctor or pharmacist before taking this product.
- if you have ever had an allergic reaction to this product or any of its ingredients

Ask a doctor before use if you have

- cough that occurs with too much phlegm (mucus)
- difficulty in urination due to enlargement of the prostate gland
- a breathing problem such as emphysema or chronic bronchitis
- persistent or chronic cough such as occurs with smoking, asthma, or emphysema
- liver disease
- glaucoma

Ask a doctor or pharmacist before use if you are

- taking sedatives or tranquilizers
- taking the blood thinning drug warfarin

When using this product

- do not exceed recommended dosage
- excitability may occur, especially in children
- avoid alcoholic beverages
- marked drowsiness may occur
- alcohol, sedatives, and tranquilizers may increase drowsiness
- use caution when driving a motor vehicle or operating machinery

Stop use and ask a doctor if

- pain or cough gets worse or lasts more than 7 days
- fever gets worse or lasts more than 3 days
- redness or swelling is present
- new symptoms occur
- cough comes back or occurs with rash or headache that lasts. These could be signs of a serious condition.

If pregnant or breast-feeding,

ask a health professional before use.

Keep out of reach of children.

In case of overdose, get medical help or contact a Poison Control Center right away. Prompt medical attention is critical for adults as well as for children even if you do not notice any signs or symptoms.

Directions

- do not take more than directed
- do not take more than 4 doses in any 24-hour period
- mL = milliliter
- only use the dose cup provided
- adults and children 12 years and over: 20 mL in dosing cup provided every 4 hours
- children under 12 years: do not use

Other information

- store at 25°C (77°F); excursions permitted between 15°-30°C (59°-86°F)
- use by expiration date on package

Inactive ingredients

anhydrous citric acid, FD&C blue #1, FD&C red #40, FD&C yellow #6, flavors, glycerin, propylene glycol, purified water, sodium benzoate, sucralose, xanthan gum

Principal display panel

♥CVS
Health®

Compare to the
active ingredients in
Mucinex® FAST-MAX®
Severe Congestion & Cough*

MAXIMUM STRENGTH
Severe Congestion
& Cough Relief

DEXTROMETHORPHAN HBr -
Cough suppressant
GUAIFENESIN - Expectorant
PHENYLEPHRINE HCl -
Nasal decongestant

Multi-Symptom
• Controls cough
• Relieves nasal &
chest congestion
• Thins & loosens mucus

For Ages 12 & Over

Mixed Berry
Flavor

♥CVS
Health®

Compare to the
active ingredients in
Mucinex® NIGHTSHIFT®
Cold & Flu*

Nighttime
Cold & Flu Relief

ACETAMINOPHEN -
Pain reliever/Fever reducer
DEXTROMETHORPHAN HBr -
Cough suppressant
TRIPROLIDINE HCl -
Antihistamine

Multi-Symptom
• Relieves cough
& sore throat
• Reduces fever
• Relieves runny
nose & sneezing

For Ages 12 & Over

Mixed Fruit
Flavor

TWO - 6 FL OZ (177 mL) BOTTLES / TOTAL 12 FL OZ (355 mL)

TAMPER EVIDENT: DO NOT USE IF IMPRINTED
SAFETY SEAL UNDER CAP IS BROKEN OR MISSING

PARENTS:
Learn about teen medicine abuse
www.StopMedicineAbuse.org

Do not take Severe Congestion & Cough Relief
and Cold & Flu Relief at the same time.

Distributed by:
CVS Pharmacy, Inc.
One CVS Drive
Woonsocket, RI 02895
© 2023 CVS/pharmacy
CVS.com® 1-800-SHOP CVS V-19849

*This product is not manufactured or
distributed by RB Health (US) LLC, owner
of the registered trademark Mucinex®
FAST-MAX® Severe Congestion & Cough
and Mucinex® NIGHTSHIFT® Cold & Flu.
50844 REV0423A00406345

CVS_44-004063_REV0423A